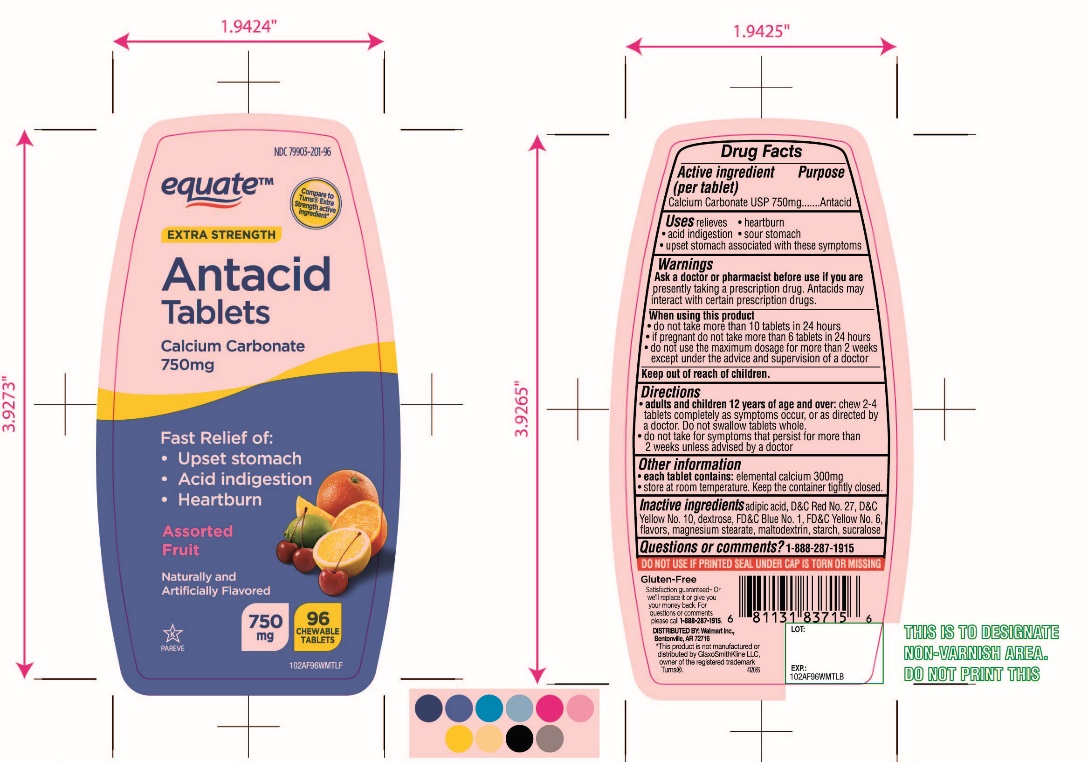 DRUG LABEL: equate Extra Strength

NDC: 79903-201 | Form: TABLET, CHEWABLE
Manufacturer: Wal-Mart Stores,Inc.,
Category: otc | Type: HUMAN OTC DRUG LABEL
Date: 20251027

ACTIVE INGREDIENTS: CALCIUM CARBONATE 750 mg/1 1
INACTIVE INGREDIENTS: ADIPIC ACID; FD&C BLUE NO. 1; DEXTROSE, UNSPECIFIED FORM; MAGNESIUM STEARATE; D&C RED NO. 27; MALTODEXTRIN; STARCH, CORN; SUCRALOSE; FD&C YELLOW NO. 6; D&C YELLOW NO. 10

equate Extra Strength Antacid Calcium Carbonate Chewable Tablets

Active ingredient (per tablet)

Calcium Carbonate USP 750mg

Purpose

Antacid

Uses

relieves

- heartburn
- acid indigestion
- sour stomach
- upset stomach associated with these symptoms

Warnings

Ask a doctor or pharmacist before use if you arepresently taking a prescription drug. Antacids may interact with certain prescription drugs.

When using this product

- do not take more than 10 tablets in 24 hours
- If pregnant do not take more than 6 tablets in 24 hours
- do not use the maximum dosage for more than 2 weeks except under the advice and supervision of a doctor

Directions

- adults and children 12 years of age and over:chew 2-4 tablets as symptoms occur, or as directed by a doctor
- do not take for symptoms that persist for more than 2 weeks unless advised by a doctor

Other information

- each tablet contains:elemental calcium 300mg
- store at room temperature. Keep the container tightly closed.

Inactive ingredients

adipic acid, D&C Red No. 27, D&C Yellow No. 10, FD&C Yellow No. 6, flavors, dextrose, magnesium stearate, maltodextrin, starch, sucralose.

Questions?

1-888-287-1915

Package/Label Principal Display Panel

NDC 79903-201-96

equate™

Compare to Tums® Extra Strength Active Ingredient*

Extra strength

Antacid

Calcium Carbonate

Starts working in Seconds to Relieve:

- Upset stomach
- Acid indigestion
- Heartburn

Assorted Fruit Flavors

750 mg

96 CHEWABLE TABLETS

Gluten-Free

Satisfaction guaranteed-

For questions or comments, please call

1-888-287-1915

Distributed by: Wal-Mart Stores, Inc.,

Bentonville,AR 72716

SAFETY SEALED: DO NOT USE IF PRINTED SEAL UNDER CAP IS TORN OR MISSING

*This product is not manufactured or distributed by GlaxoSmithKline LLC, owner of the registered trademark,Tums®.